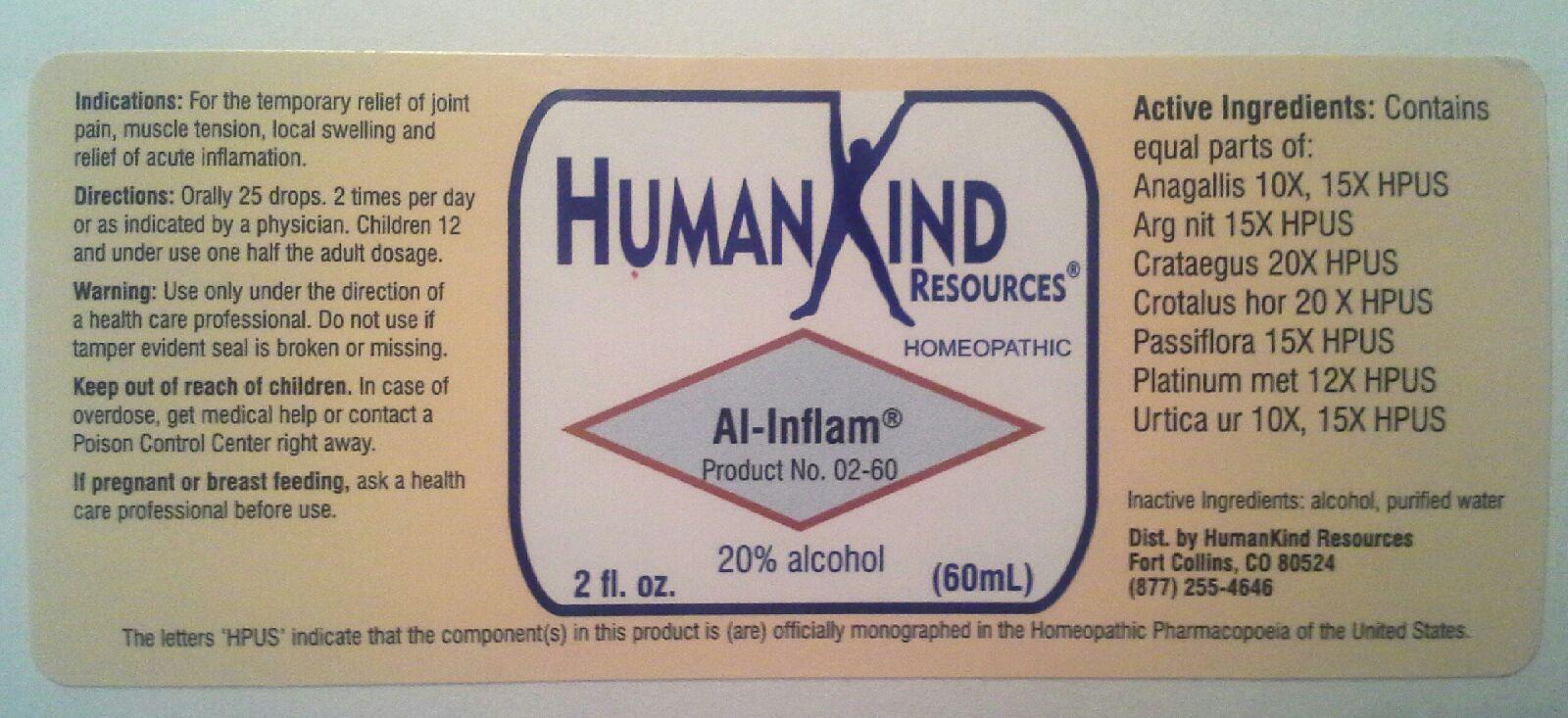 DRUG LABEL: Al-Inflam
NDC: 64616-080 | Form: LIQUID
Manufacturer: Vitality Works, Inc.
Category: homeopathic | Type: HUMAN OTC DRUG LABEL
Date: 20251217

ACTIVE INGREDIENTS: ANAGALLIS ARVENSIS 10 [hp_X]/1 mL; SILVER NITRATE 15 [hp_X]/1 mL; HAWTHORN LEAF WITH FLOWER 20 [hp_X]/1 mL; CROTALUS HORRIDUS HORRIDUS VENOM 20 [hp_X]/1 mL; PASSIFLORA INCARNATA FLOWERING TOP 15 [hp_X]/1 mL; PLATINUM 12 [hp_X]/1 mL; URTICA URENS 10 [hp_X]/1 mL
INACTIVE INGREDIENTS: WATER; ALCOHOL

Al-Inflam

Al-Inflam

Anagalis 10X, 15X

Arg nit 15X

Crataegus 20X

Crotalus hor 20X

Passiflora 15X

Platinum met 12X

Urtica ur 10X, 15X

Al-Inflam

Alcohol, Purified Water

Al-Inflam

Use only under the direction of a health care professional. Do not use if tamper evident seal is broken or missing.

Al-Inflam

Keep out of reach of children. In case of overdose, get medical help or contact a Poison Control Center right away.

Al-Inflam

For the temporary relief of joint pain, muscle tension, local swelling and relief of acute inflamation.

Al-Inflam

Orally 25 drops, 2 times per day or as indicated by a physician. Children 12 and under use one half the adult dosage.

Al-Inflam

Assist the body in its response to injury, infection and allergy.